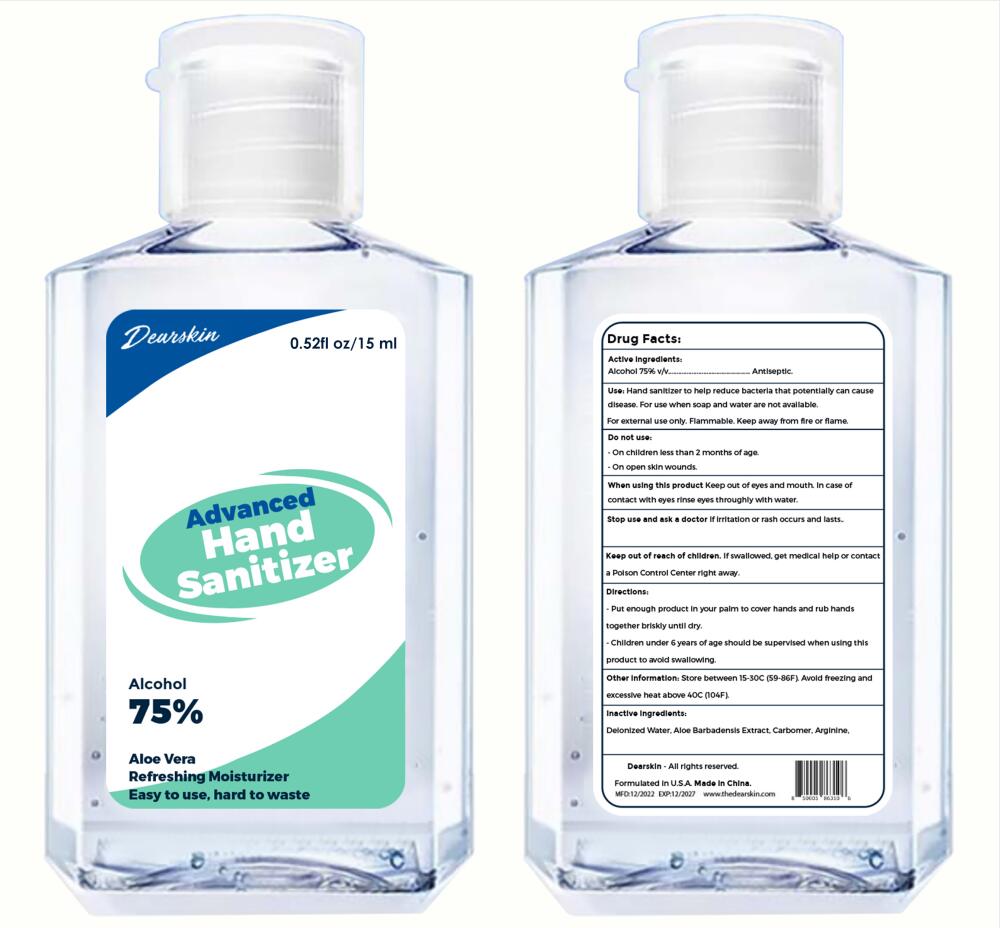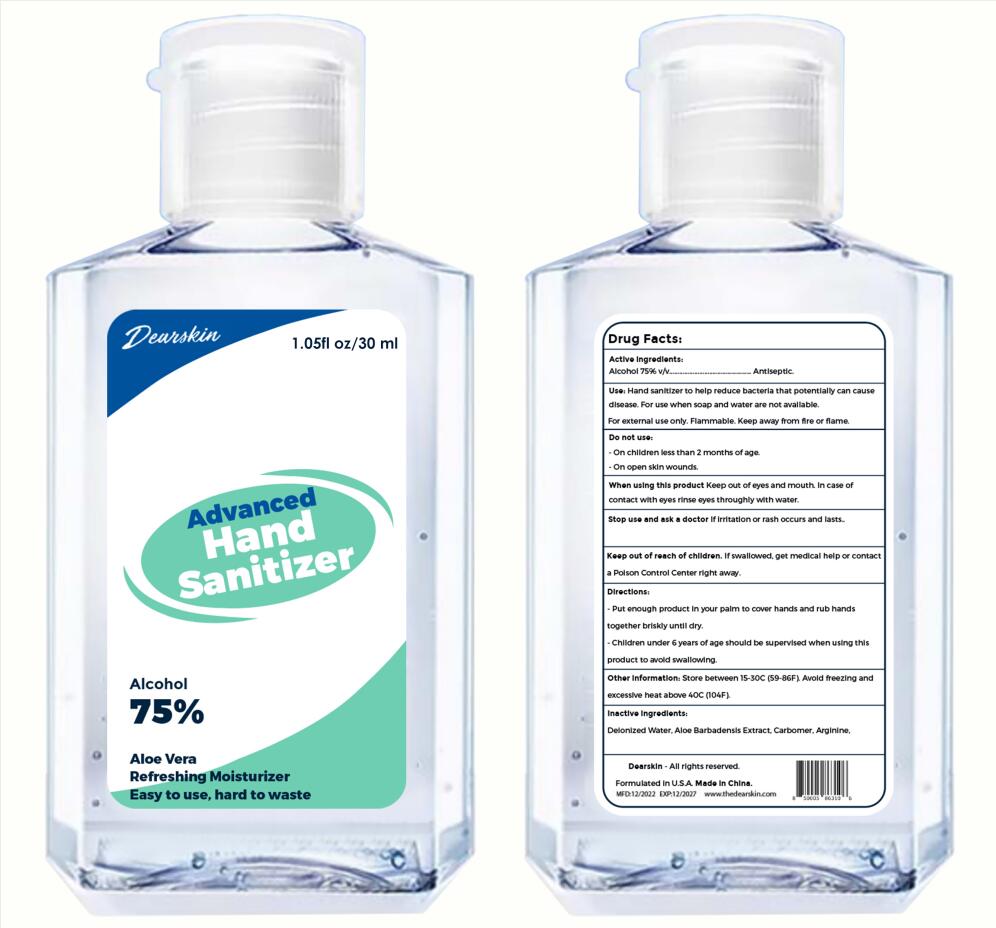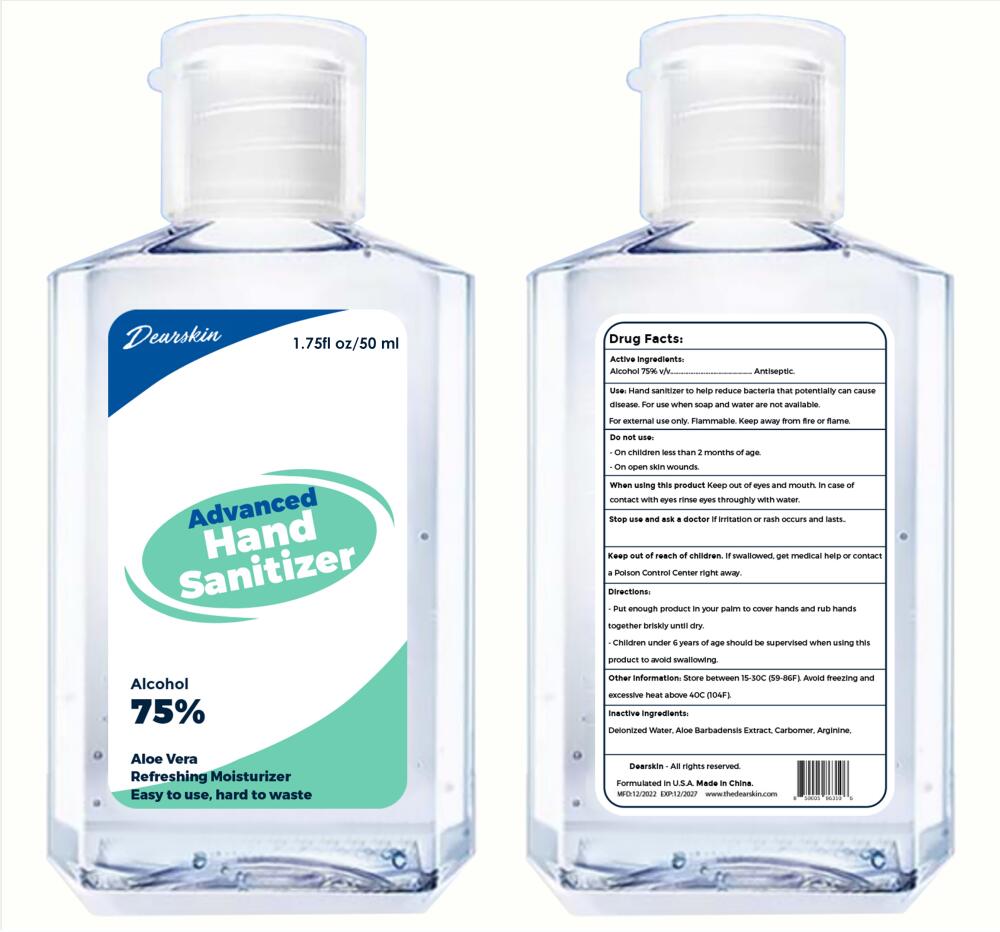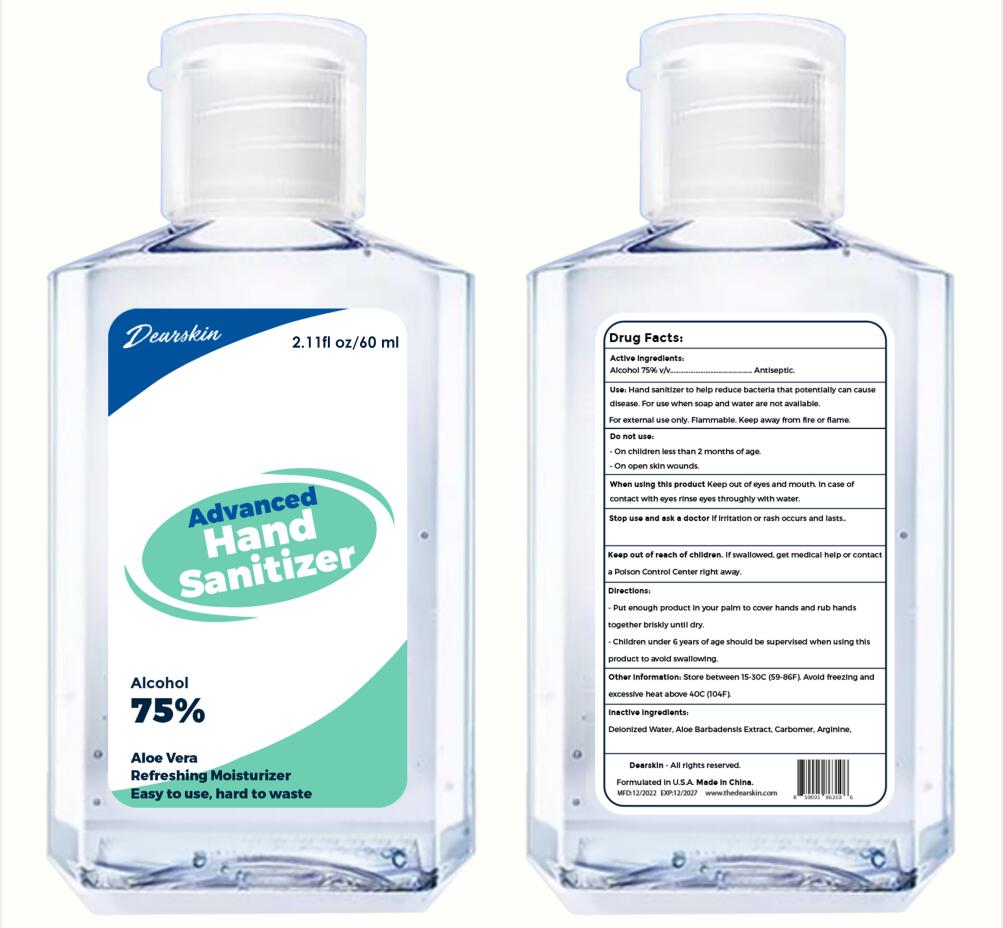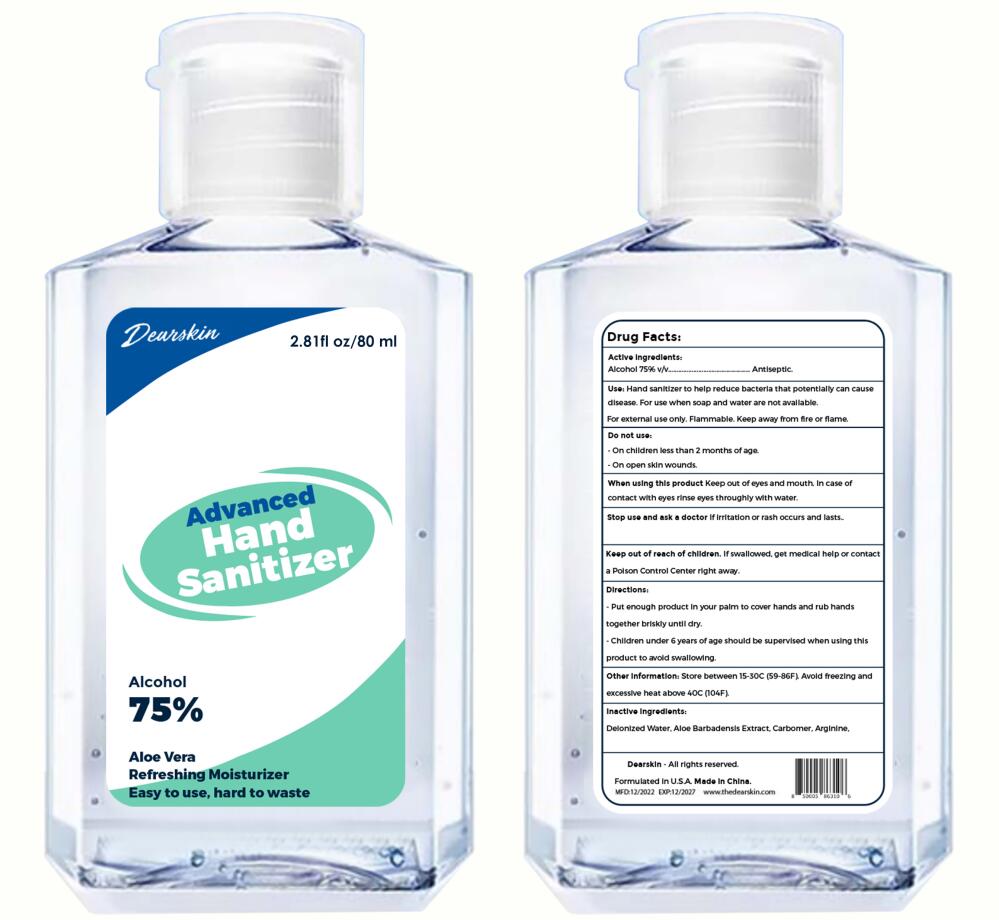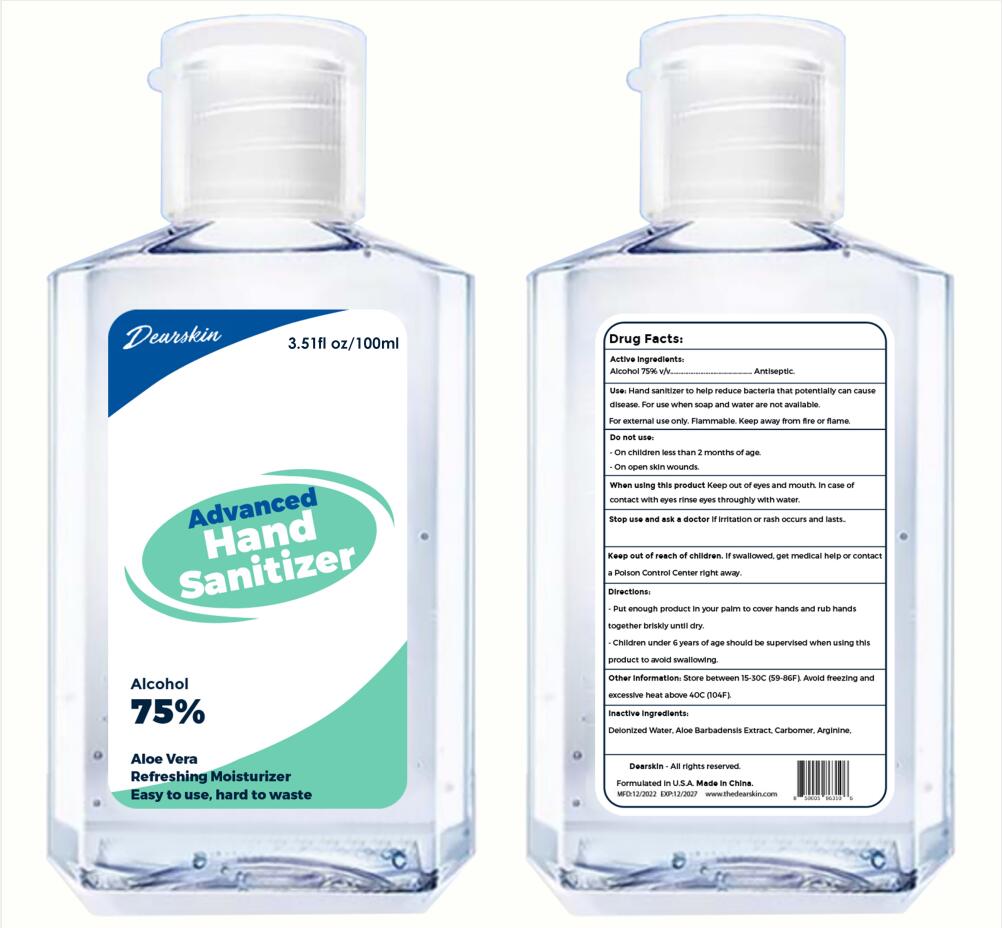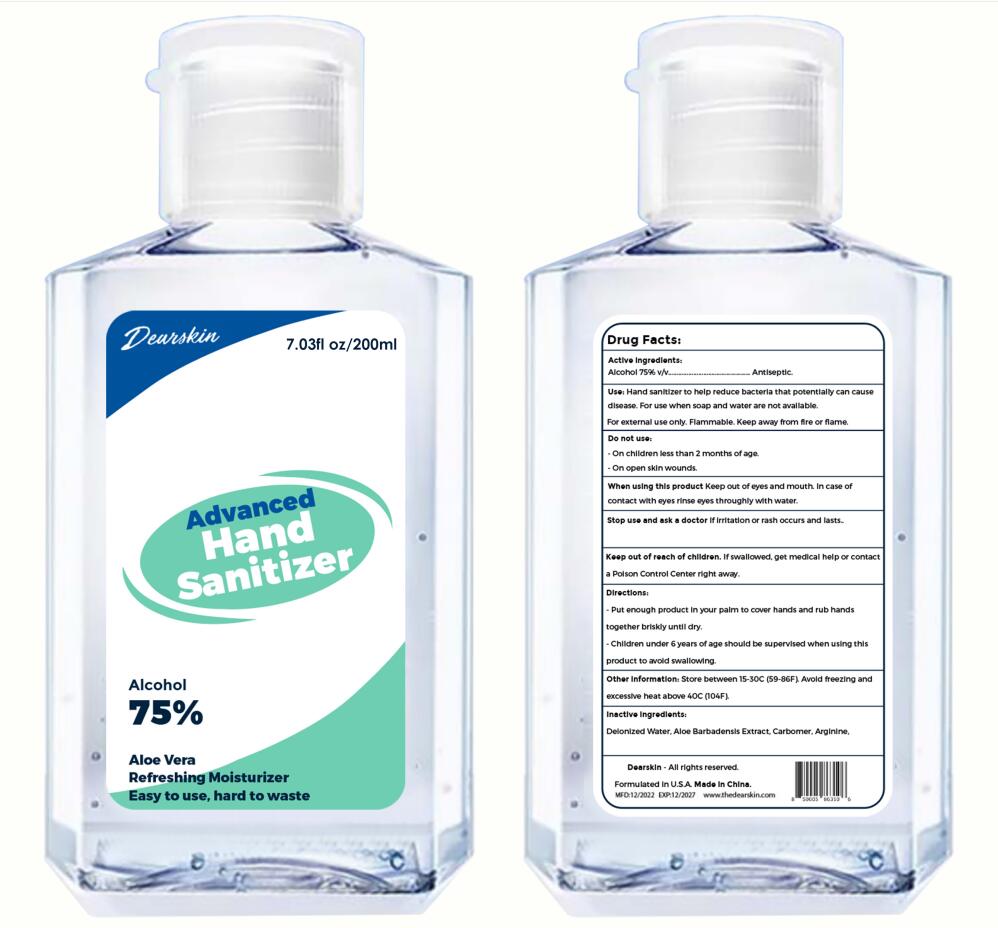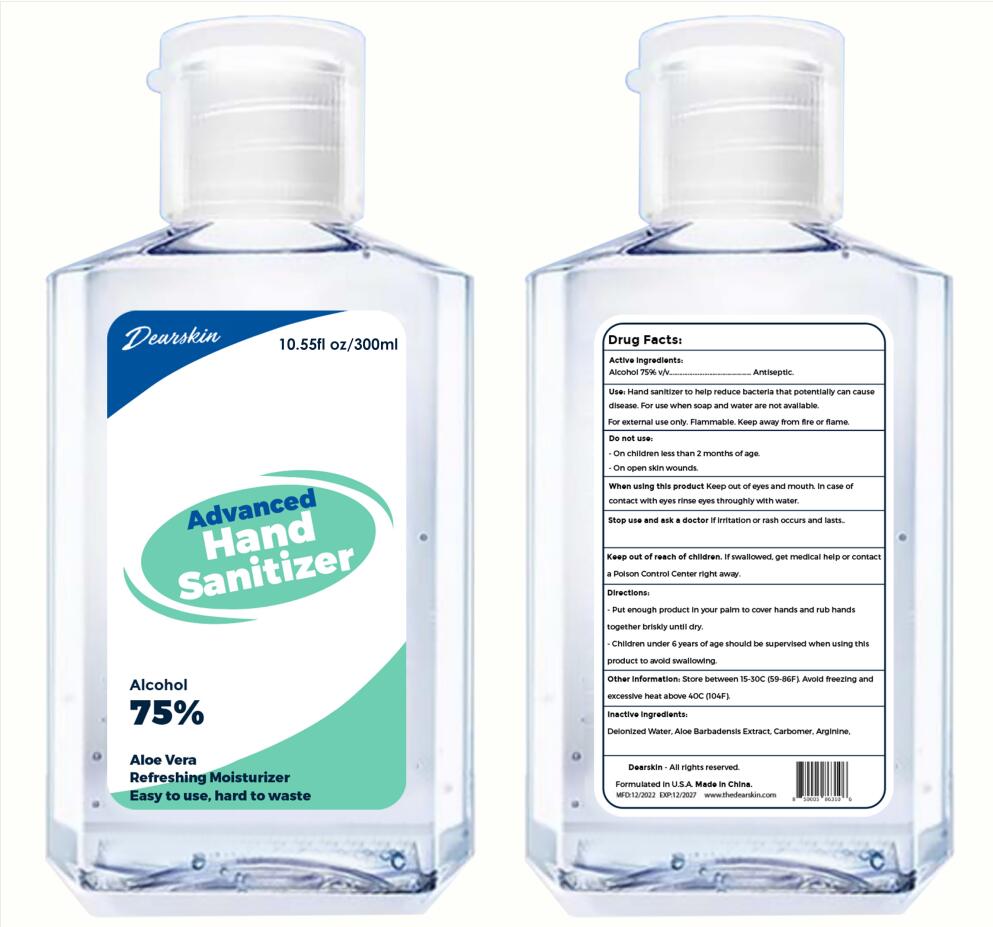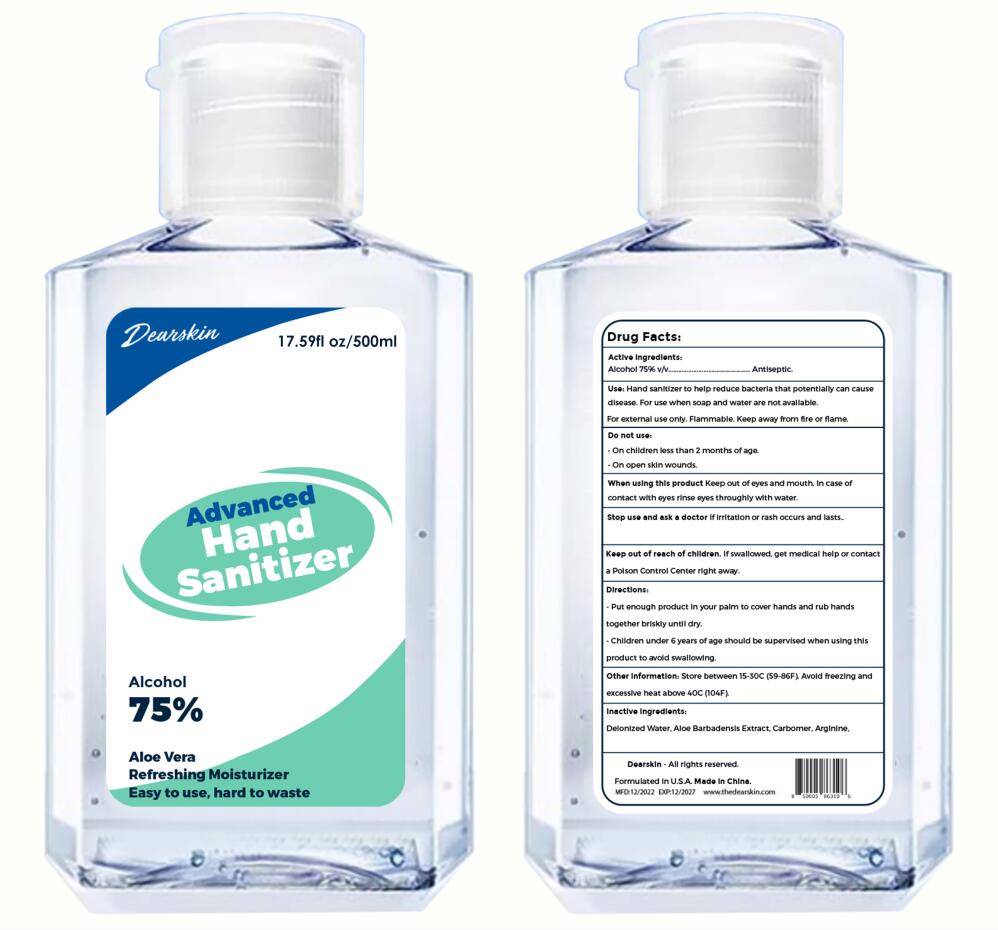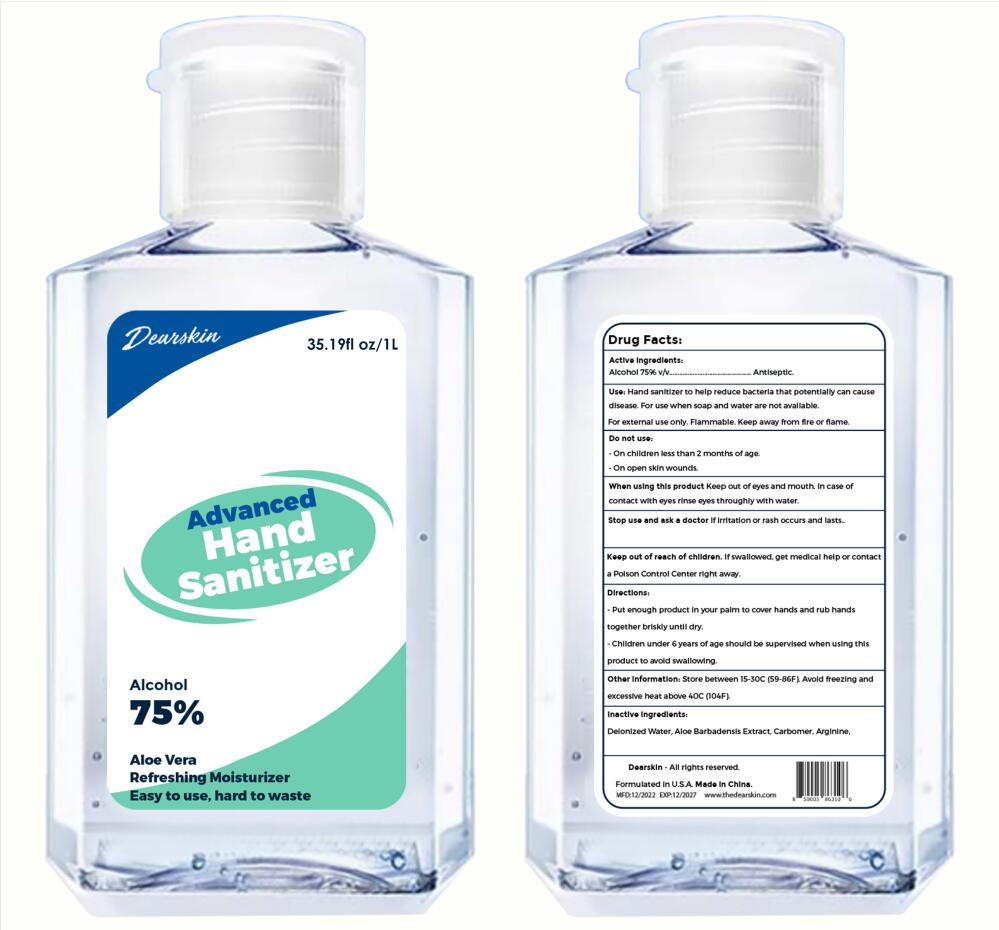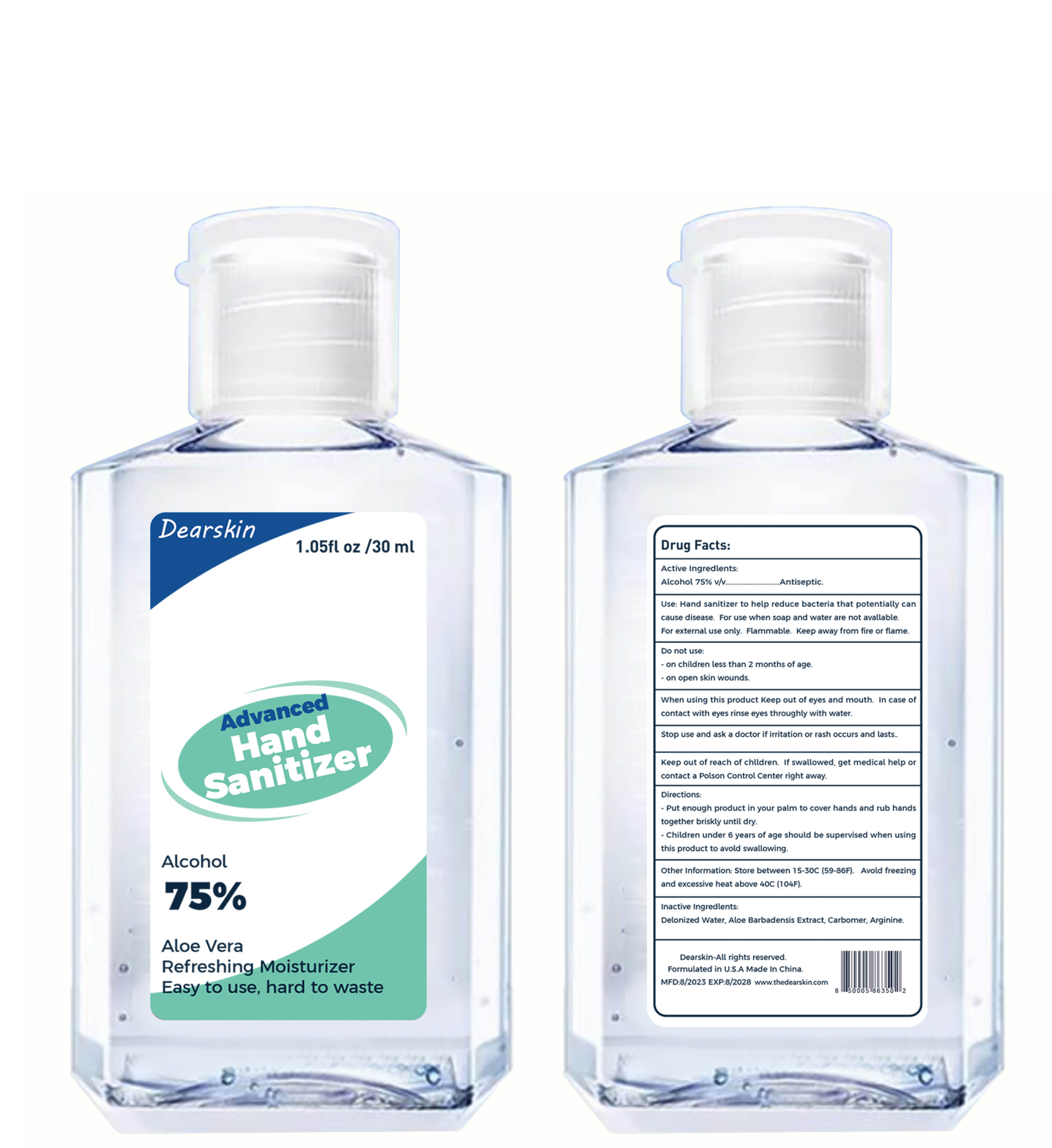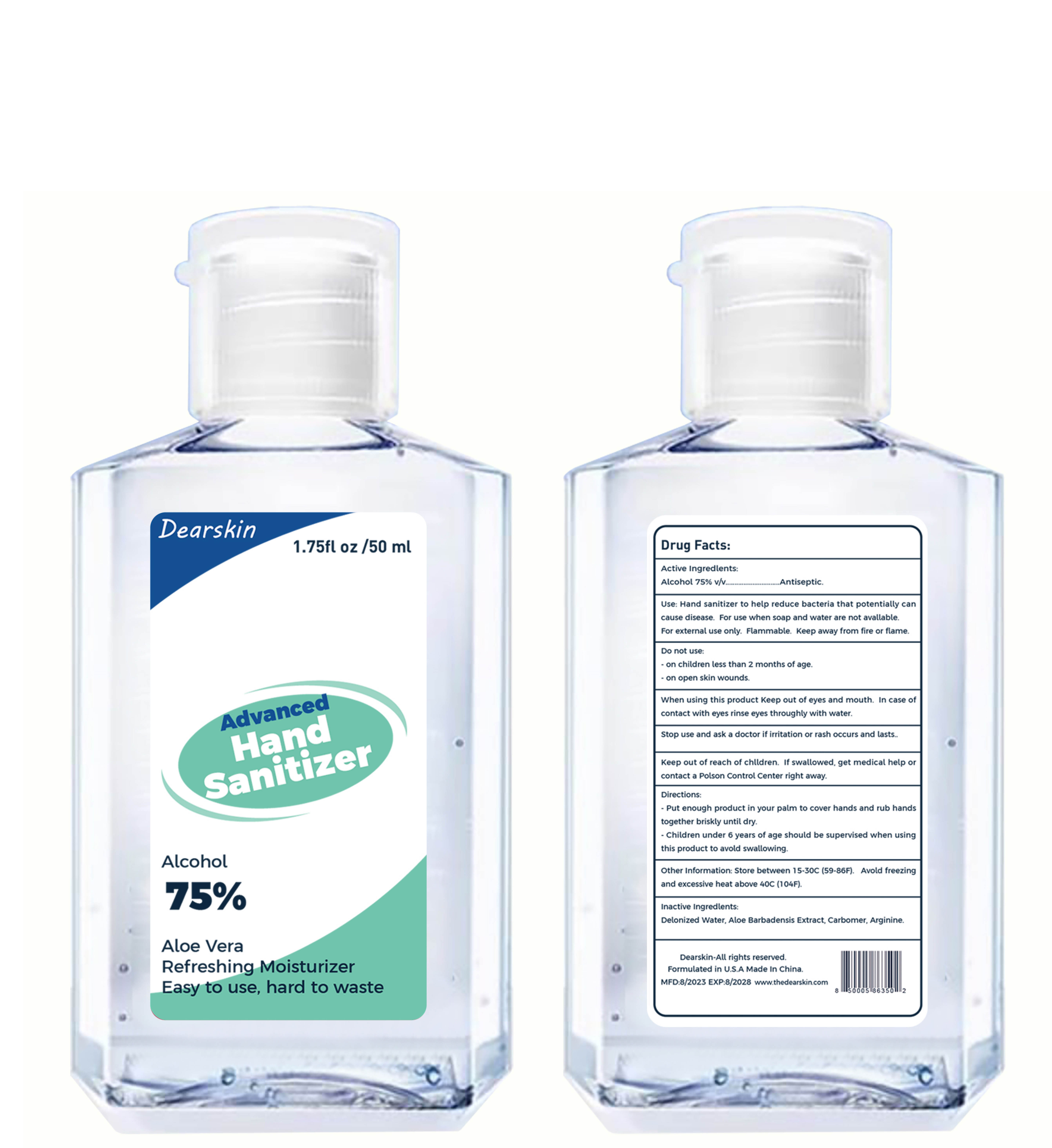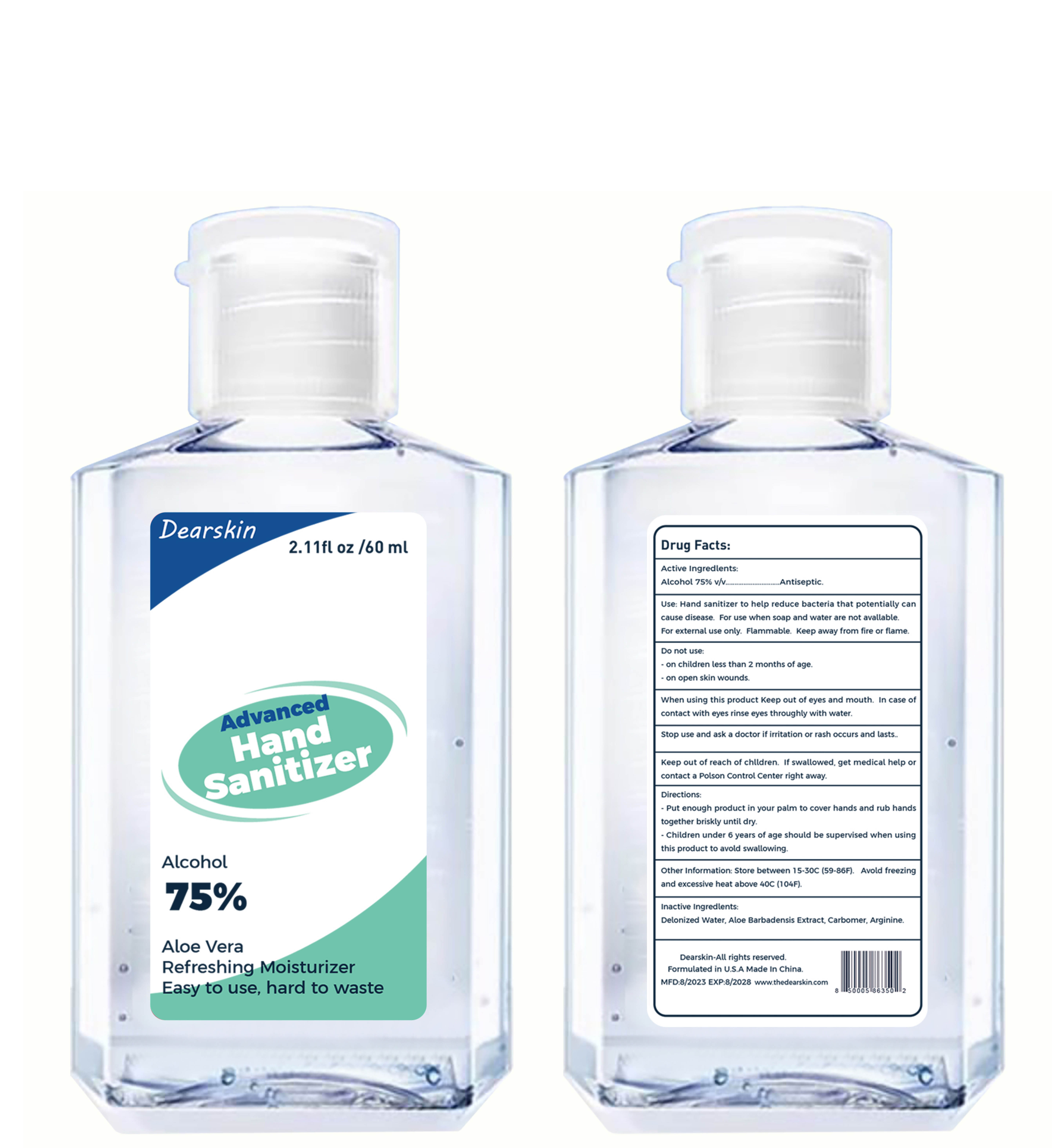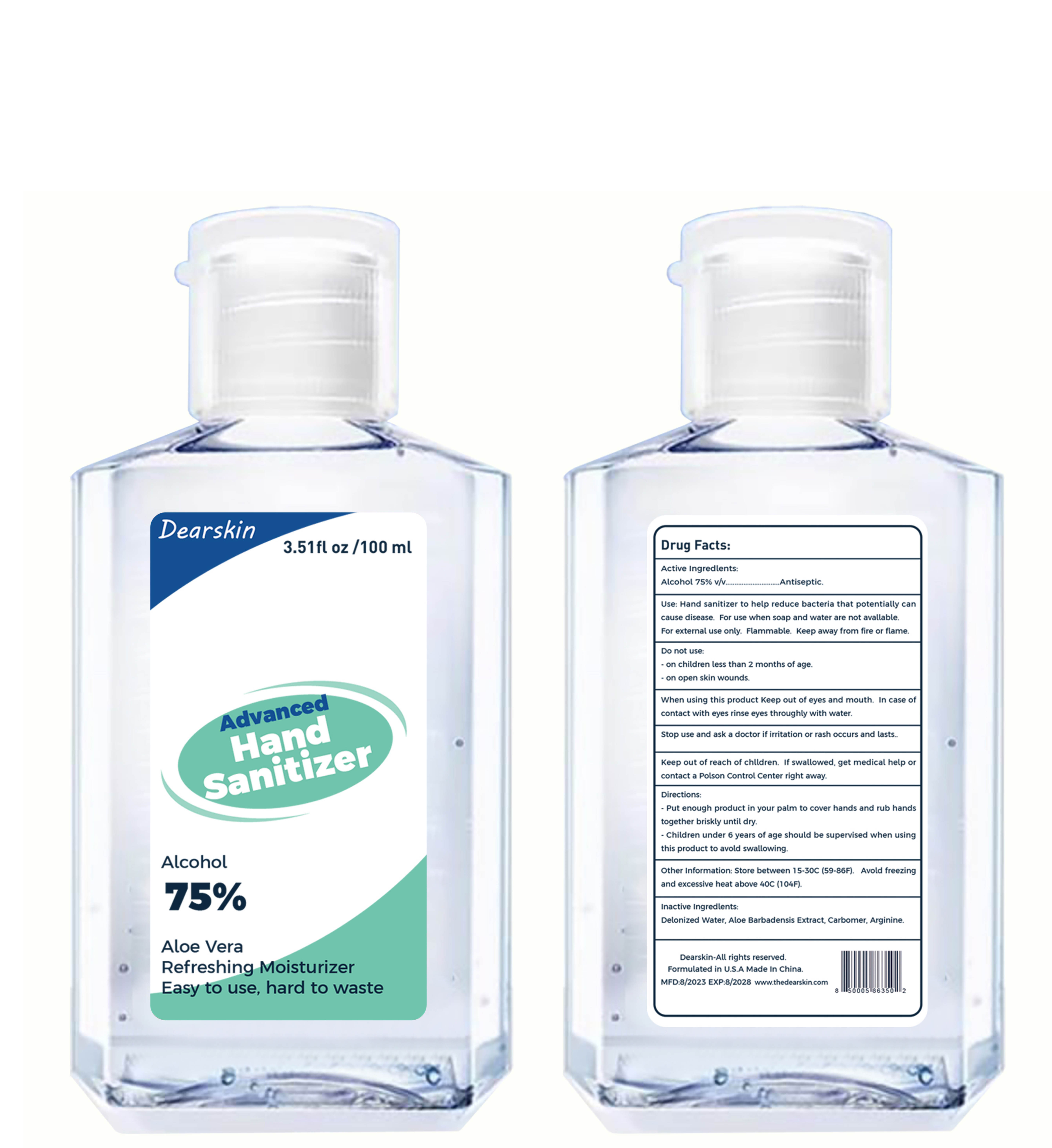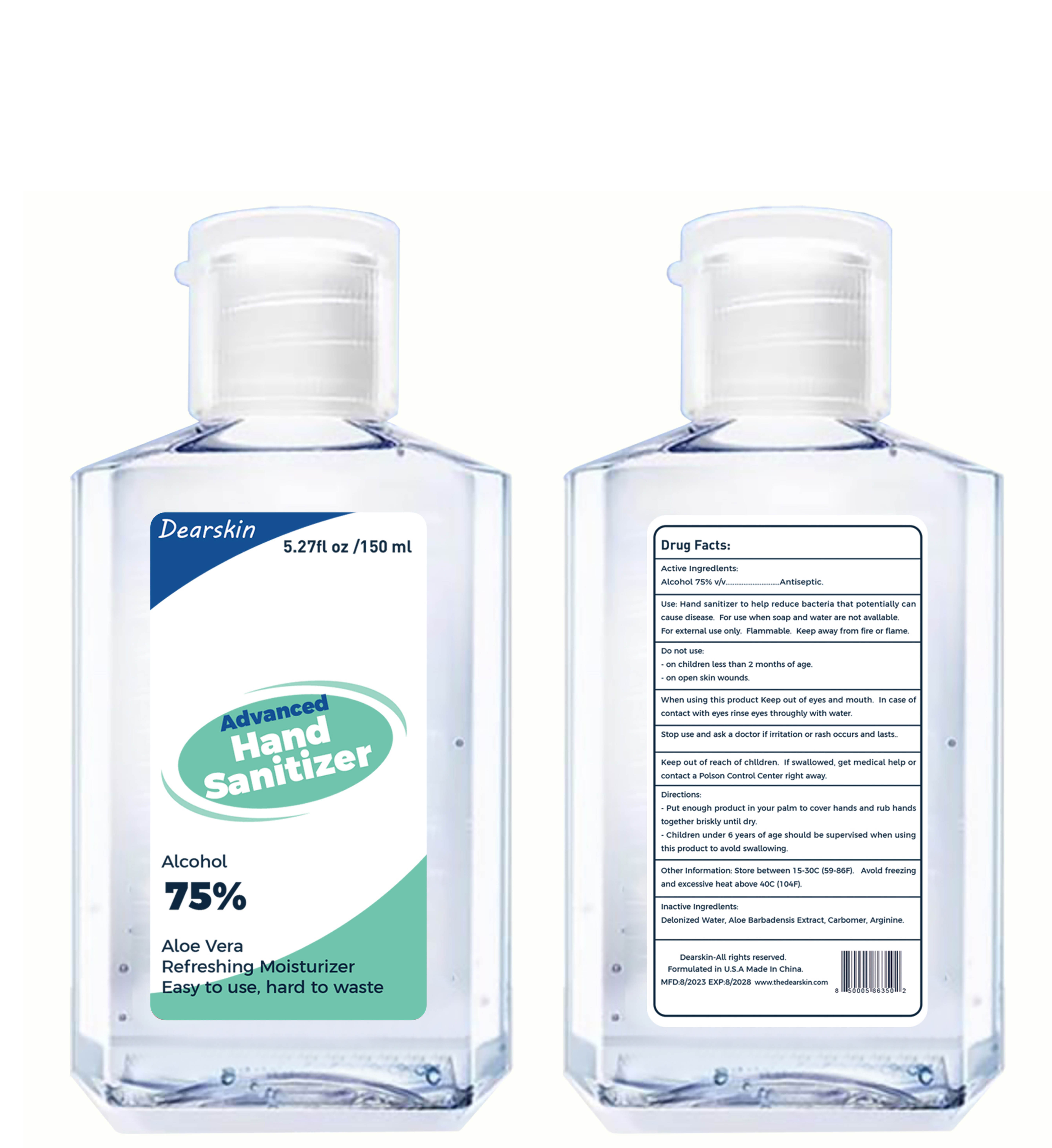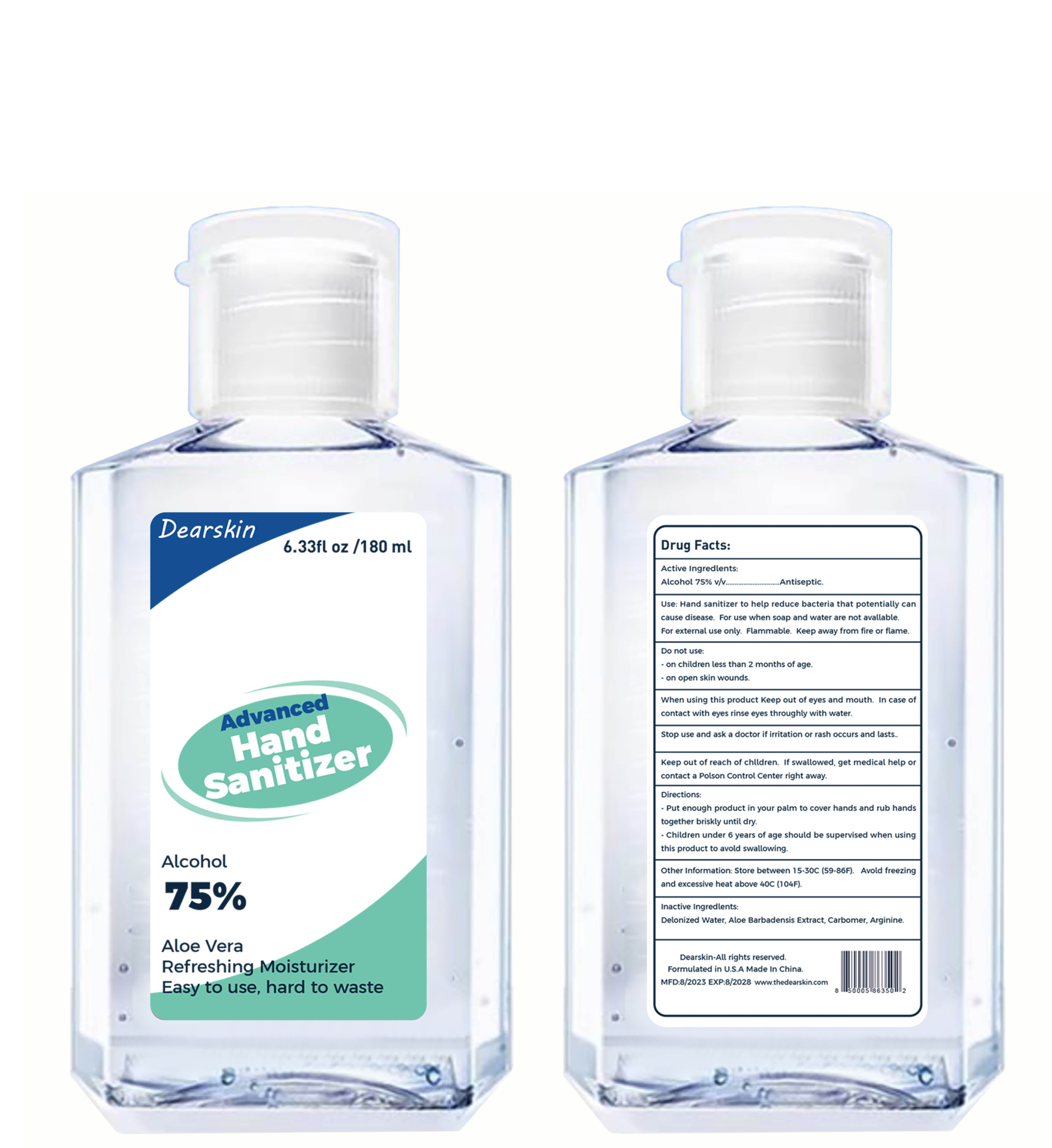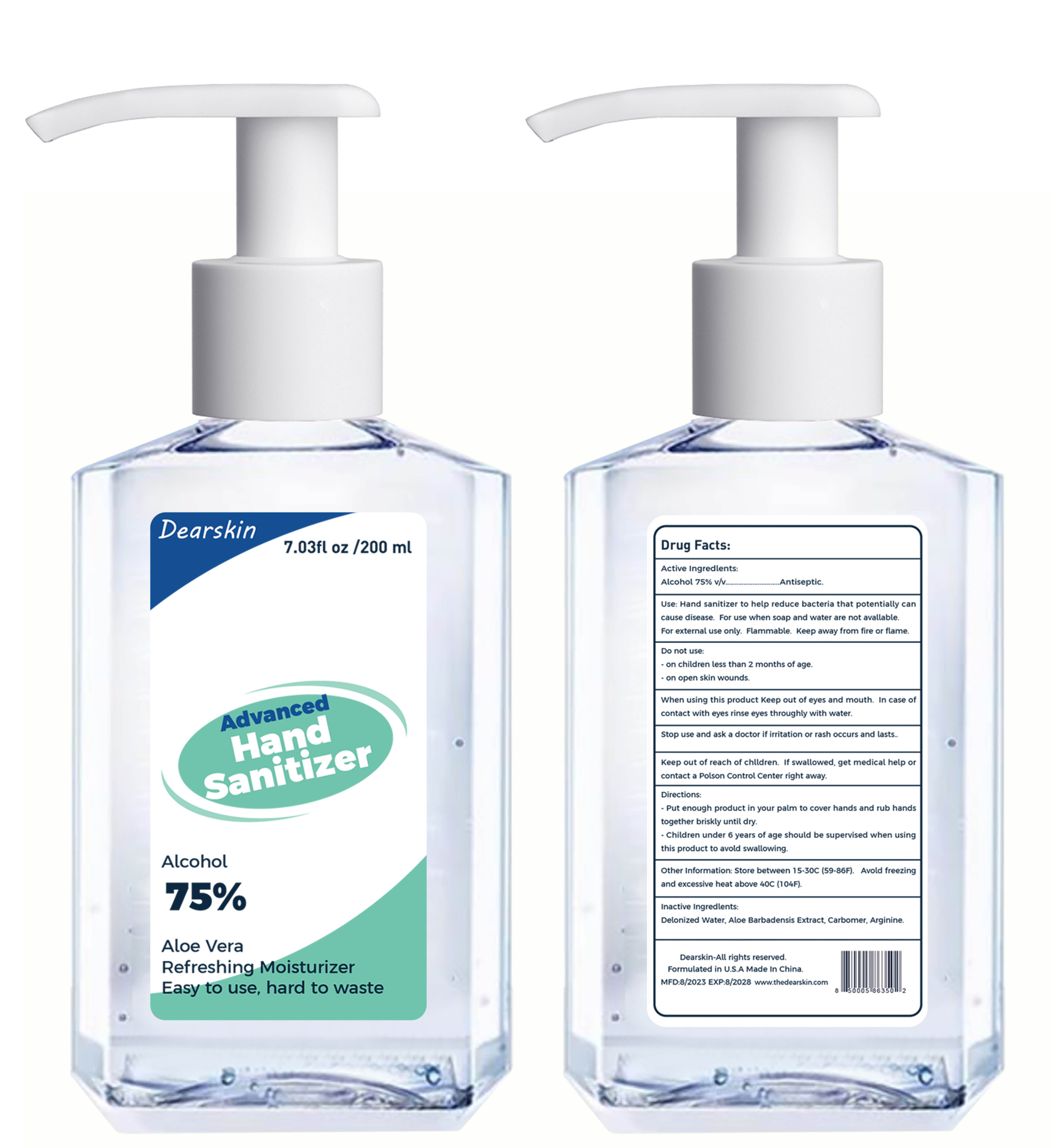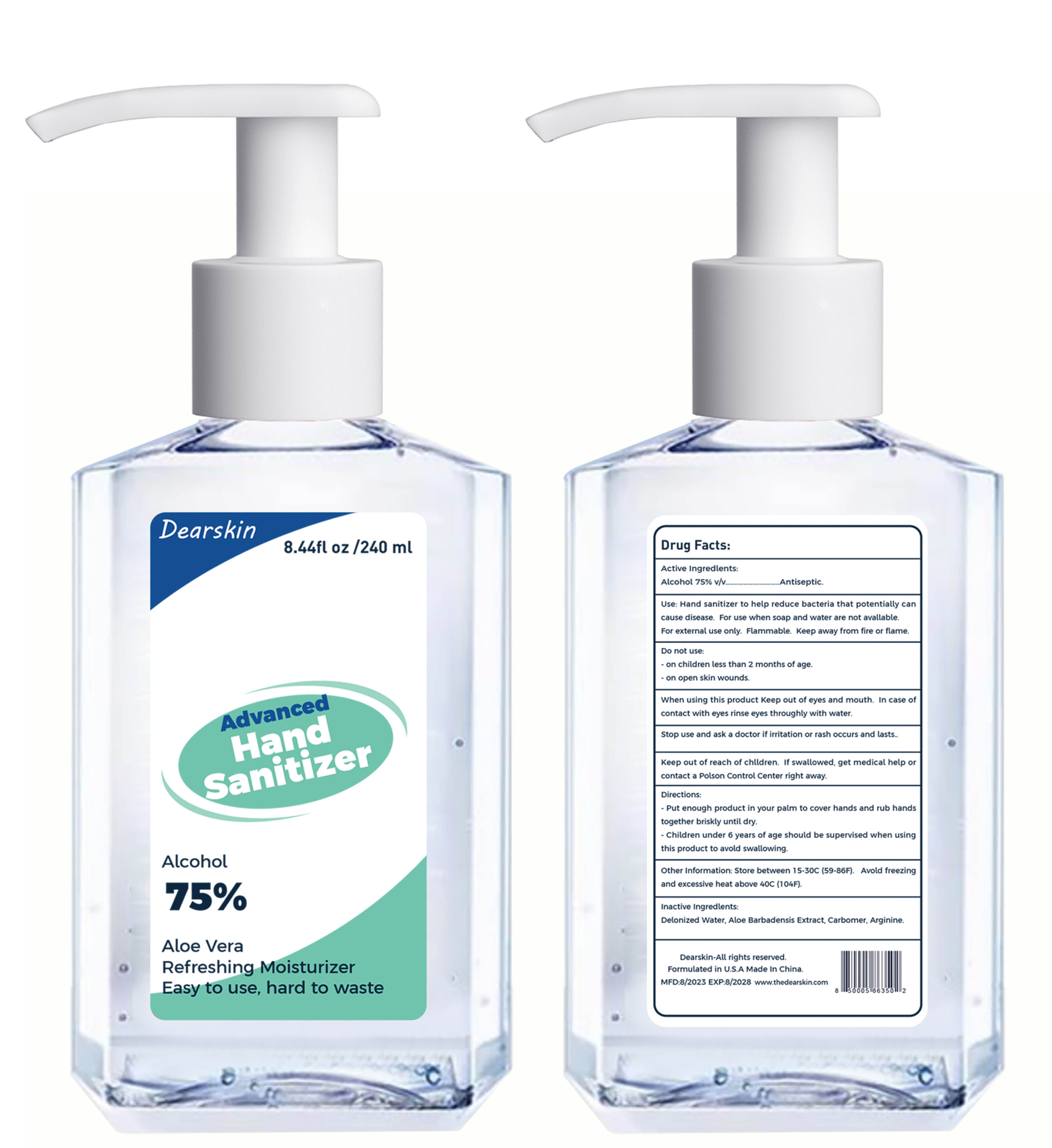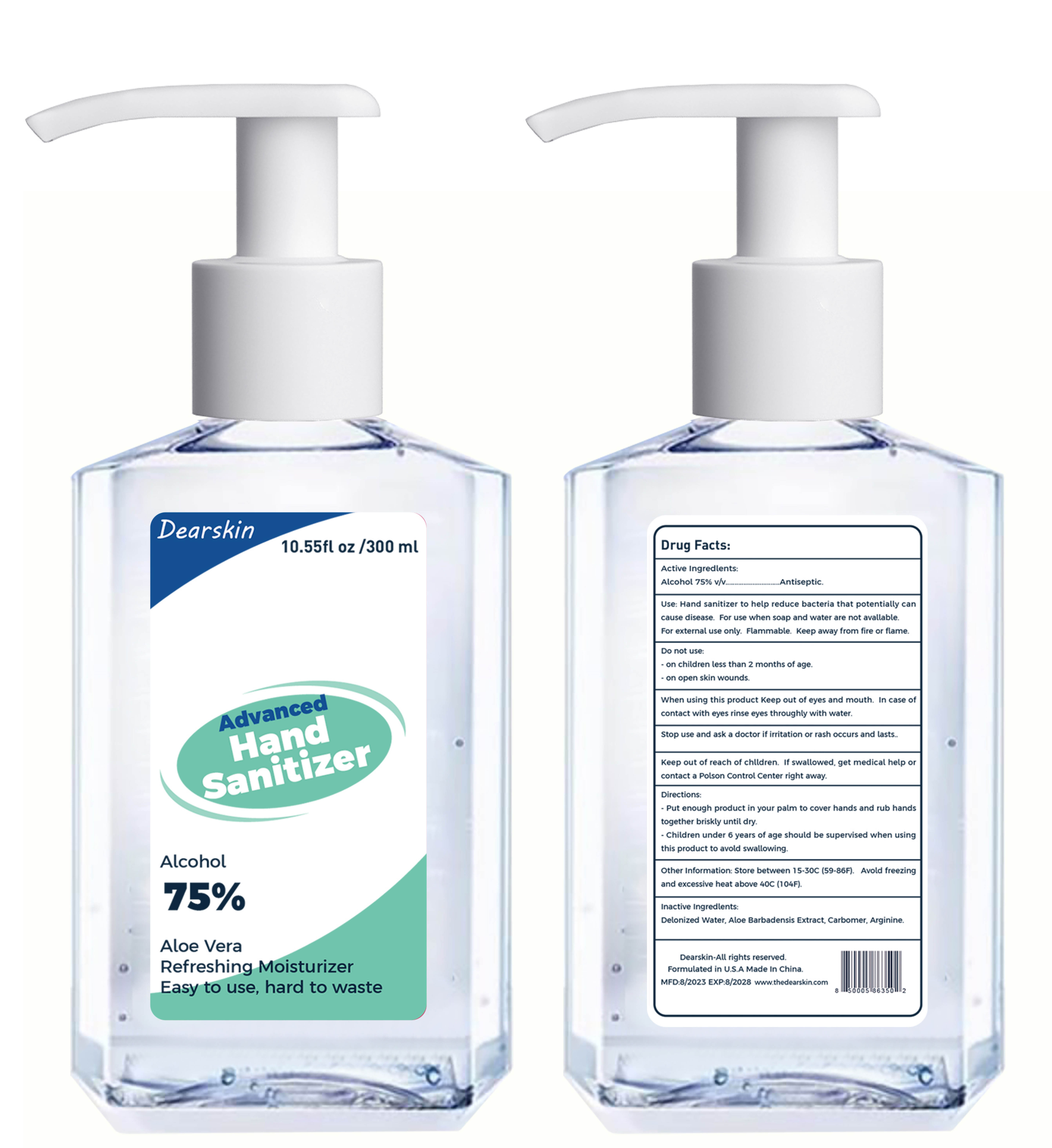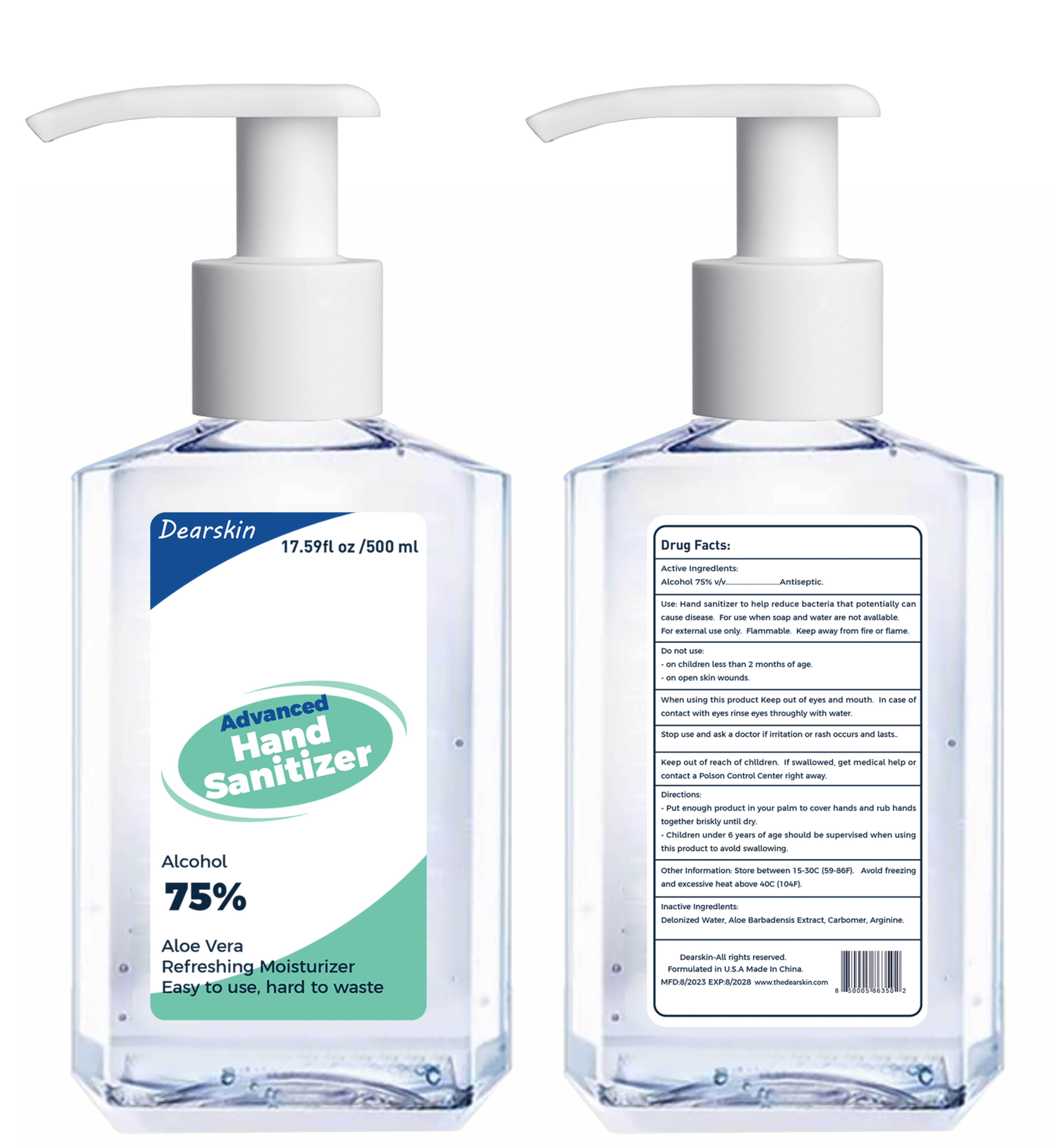 DRUG LABEL: Hand Sanitizer
NDC: 77975-010 | Form: LIQUID
Manufacturer: Guangzhou Tingcai Cosmetic Co., Ltd.
Category: otc | Type: HUMAN OTC DRUG LABEL
Date: 20230823

ACTIVE INGREDIENTS: ALCOHOL 75 mL/100 mL
INACTIVE INGREDIENTS: CARBOMER HOMOPOLYMER, UNSPECIFIED TYPE; WATER; ARGININE; ALOE VERA LEAF

77975-010
Hand Sanitizer

Active Ingredient(s)

Alcohol 75%

Purpose

Antiseptic

Use

Hand sanitizer to help reduce bacteria that potentially can causedisease. For use when soap and water are not avallableFor external use only. Flammable. Keep away from fire or flame.

Warnings

Flammable. Keep away from fire or flame.
For external use only.

Do not use

On children less than 2 months of age.

On open skin wounds

When using this product Keep out of eyes and mouth In case of contact with eyes rinse eyes throughly with water.

stop use and ask a doctor If Irritation or rash occurs and lasts.

KEEP OUT OF REACH OF CHILDREN

Keep out of reach of chlldren . If swallowed . get medical help or contacta Polson Control center right away.

Directions

Put enough product In your palm to cover hands and rub handstogether briskly until dry.

Children under 6 years of age should be supervised when using thlsproduct to avold swallowing.

Other information

Store between 15-30C (59-86F). Avold freezing andexcessive heat above 40C(104F).

Inactive ingredients

Delonlzed Water, Aloe Barbadensis Extract, Carbomer, Arginine.